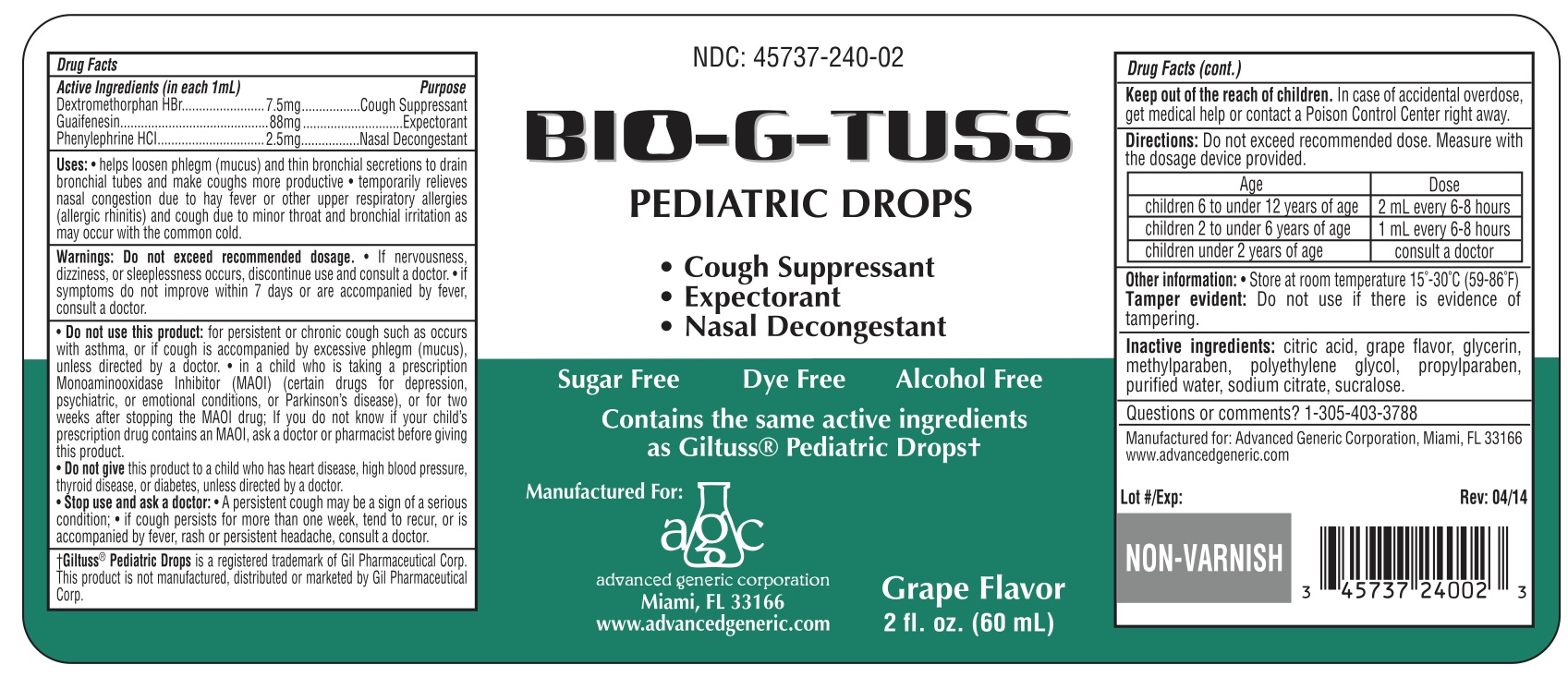 DRUG LABEL: Bio-G-Tuss
NDC: 45737-240 | Form: SOLUTION/ DROPS
Manufacturer: Advanced Generic Corporation
Category: otc | Type: HUMAN OTC DRUG LABEL
Date: 20241220

ACTIVE INGREDIENTS: DEXTROMETHORPHAN HYDROBROMIDE 7.5 mg/1 mL; GUAIFENESIN 88 mg/1 mL; PHENYLEPHRINE HYDROCHLORIDE 2.5 mg/1 mL
INACTIVE INGREDIENTS: ANHYDROUS CITRIC ACID; GLYCERIN; METHYLPARABEN; POLYETHYLENE GLYCOL, UNSPECIFIED; PROPYLPARABEN; WATER; SODIUM CITRATE; SUCRALOSE

AGC-BioGTuss Ped Dr 240

Active ingredients

Dextromethorphan HBr

Guaifenesin

Phenylephrine HCl

Purpose

Cough Suppressant

Expectorant

Nasal Decongestant

Uses

- helps lossen phlegm (mucus) and thin bronchial secretions to drain broncial tubes and make coughs more productive
- temporarily relieves nasal congestion due to hay fever or other respiratory allergies (allergic rhinitis) and cough due to minor throat and bronchial irritation as may occur with the common cold

Warnings

Do not exceed recommended dosage

- If nervousness dizziness, or sleeplessness ocurs, discontinue use and consult a doctor
- If symptoms do not improve wihtin 7 days or are accompanied by fever, consult a doctor.

Do not use this product

- for persistant or chronic cough such as occurs with asthma, or if cough is accompanied by excessive phlegm (mucus), unless directed by a doctor
- in a child who is taking a prescription Monoaminooxidase Inhibitor (MAOI) (certain drugs for depression, psychiatric, or emotional conditions, or Parkinson's disease), or for two weeks after stopping the MAOI drug; if you do not know if your child's prescription drug contains an MAOI, ask a doctor or pharmacist before giving this product.
- Do not give this product to a child who has heart disease, high blood pressure, thyroid disease, or diabetes, unless directed by a doctor.

Stop use and ask a doctor

- A persistent cough may be a sign of a serious condition
- if cough persists for more than onweek, tend to recur, or is accompanied by fever, rash or persistent headache, consult a doctor.

Keep out of reach of children. In case of accidental overdose, get medical help or contact a Poison Control Center right away.

Directions

Age | Dose
children 6 to under 12 years of age | 2 mL every 6-8 hours
chidren 2 to under 6 years of age | 1 mL every 6-8 hours
children under 2 years of age | consult a doctor

Inactive ingredients

citric acid, grape flavor, glycerin, methylparaben, polyethylene glycol, propylparaben, purified water, sodium citrate, sucralose.

Questions or Comments

1-305-403-3788